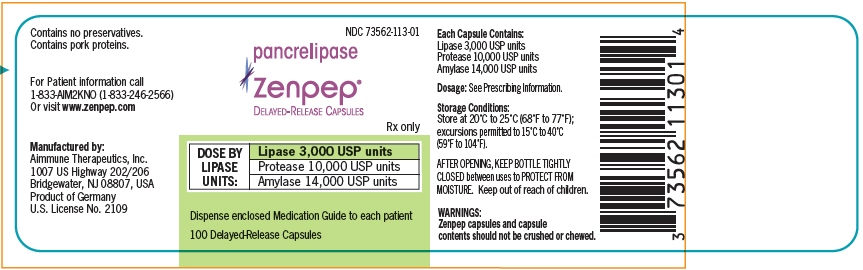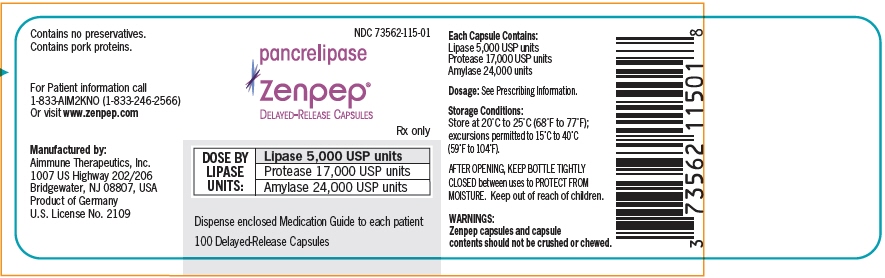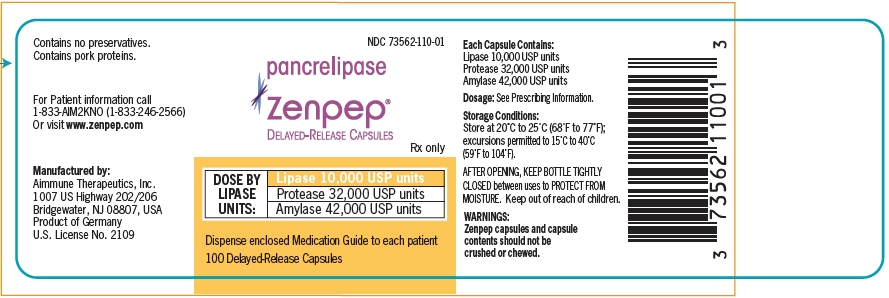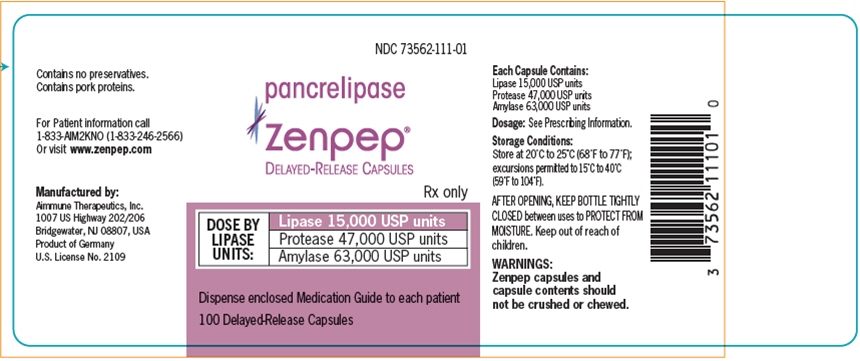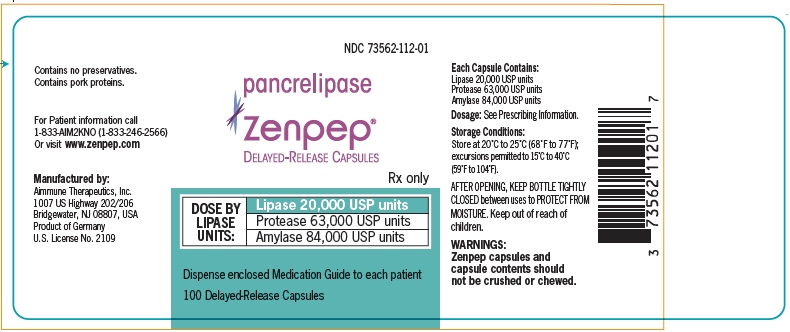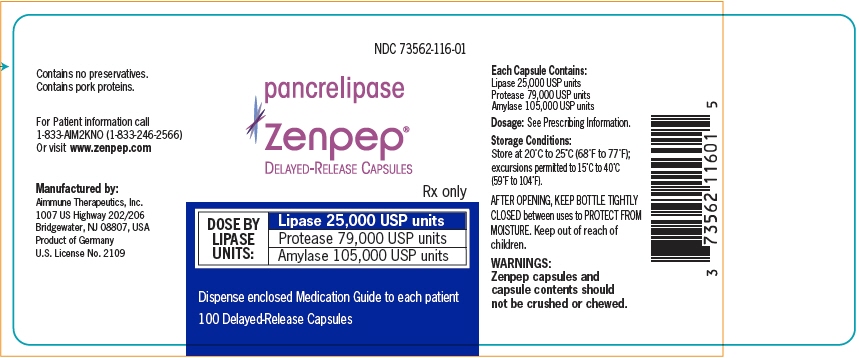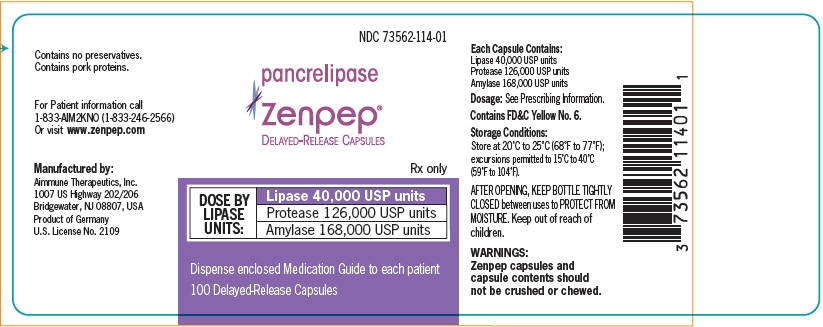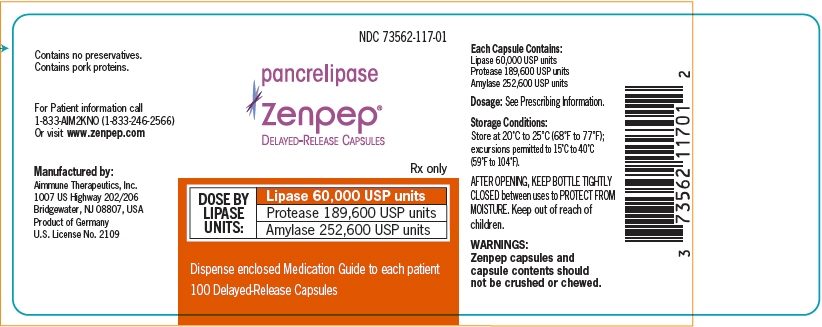 DRUG LABEL: Zenpep
NDC: 73562-113 | Form: CAPSULE, DELAYED RELEASE
Manufacturer: Aimmune Therapeutics, Inc.
Category: prescription | Type: HUMAN PRESCRIPTION DRUG LABEL
Date: 20251114

ACTIVE INGREDIENTS: PANCRELIPASE LIPASE 3000 [USP'U]/1 1; PANCRELIPASE PROTEASE 10000 [USP'U]/1 1; PANCRELIPASE AMYLASE 14000 [USP'U]/1 1
INACTIVE INGREDIENTS: CROSCARMELLOSE SODIUM; HYDROGENATED CASTOR OIL; SILICON DIOXIDE; MICROCRYSTALLINE CELLULOSE; MAGNESIUM STEARATE; TALC; TRIETHYL CITRATE; HYPROMELLOSE PHTHALATE (31% PHTHALATE, 170 CST); CARRAGEENAN; POTASSIUM CHLORIDE; TITANIUM DIOXIDE; HYPROMELLOSE, UNSPECIFIED; WATER

HIGHLIGHTS OF PRESCRIBING INFORMATION

These highlights do not include all the information needed to use ZENPEP safely and effectively. See full prescribing information for ZENPEP.
ZENPEP® (pancrelipase) delayed-release capsules, for oral use
Initial U.S. Approval: 2009

1 INDICATIONS AND USAGE

ZENPEP® is indicated for the treatment of exocrine pancreatic insufficiency in adult and pediatric patients. (1)

2 DOSAGE AND ADMINISTRATION

Important Dosing Information (2.1)

- ZENPEP is a mixture of enzymes including lipases, proteases, and amylases and dosing is based on lipase units. Dosing scheme based on actual body weight or fat ingestion.
- Individualize the dosage based on clinical symptoms, the degree of steatorrhea present, and the fat content of the diet.
- Do not exceed 2,500 lipase units/kg/meal, 10,000 lipase units/kg/day, or 4,000 lipase units/g fat ingested/day in adult and pediatric patients greater than 12 months of age without further investigation. (5.1)
- The total daily dosage in adult and pediatric patients greater than 12 months of age should reflect approximately three meals plus two or three snacks per day. With each snack, administer approximately half the prescribed dose for a meal.
- Do not substitute other pancreatic enzyme products for ZENPEP. When switching from another pancreatic enzyme product to ZENPEP, monitor patients for clinical symptoms of exocrine pancreatic insufficiency and titrate the dosage as needed.

Recommended Dosage (2.2)

Adult and Pediatric Patients Greater than 12 Months: The recommended initial starting dosage is:

- 500 lipase units/kg/meal for adult and pediatric patients 4 years of age and older.
- 1,000 lipase units/kg/meal for pediatric patients greater than 12 months of age to less than 4 years of age.

- Titrate to either 2,500 lipase units/kg/meal, 10,000 lipase units/kg/day, or 4,000 lipase units/g fat ingested/day. Higher dosages may be administered if documented effective by fecal fat measures or improvement in malabsorption.

Pediatric Patients Birth to 12 Months: The recommended dosage is 3,000 lipase units (one capsule) per 120 mL of formula or per breastfeeding.

Preparation and Administration Instructions (2.3)

- Swallow capsules whole. For patients unable to swallow intact capsule(s), the capsule contents may be sprinkled on soft acidic food (e.g., applesauce, bananas, pears).
- Do not crush or chew ZENPEP capsules or capsule contents.
- Consume sufficient liquids to ensure complete swallowing of ZENPEP. (5.2)
- See the full prescribing information for additional information on administering to pediatric patients birth to 12 months. (2.3)

3 DOSAGE FORMS AND STRENGTHS

Delayed-Release Capsules (3):

- 3,000 USP units of lipase; 10,000 USP units of protease; and 14,000 USP units of amylase
- 5,000 USP units of lipase; 17,000 USP units of protease; and 24,000 USP units of amylase
- 10,000 USP units of lipase; 32,000 USP units of protease; and 42,000 USP units of amylase
- 15,000 USP units of lipase; 47,000 USP units of protease; and 63,000 USP units of amylase
- 20,000 USP units of lipase; 63,000 USP units of protease; and 84,000 USP units of amylase
- 25,000 USP units of lipase; 79,000 USP units of protease; and 105,000 USP units of amylase
- 40,000 USP units of lipase; 126,000 USP units of protease; and 168,000 USP units of amylase
- 60,000 USP units of lipase; 189,600 USP units of protease; and 252,600 USP units of amylase

4 CONTRAINDICATIONS

None (4)

5 WARNINGS AND PRECAUTIONS

- Fibrosing Colonopathy: Associated with high doses, usually over prolonged use and in pediatric patients with cystic fibrosis. Colonic stricture reported in pediatric patients less than 12 years of age with dosages exceeding 6,000 lipase units/kg/meal. Monitor during treatment for progression of preexisting disease. Do not exceed the recommended dosage, unless clinically indicated. (2.1, 5.1)
- Irritation of the Oral Mucosa: May occur due to loss of protective enteric coating on the capsule contents. (2.3, 5.2)
- Hyperuricemia: Reported with high dosages; consider monitoring blood uric acid levels in patients with gout, renal impairment, or hyperuricemia. (5.3)
- Risk of Viral Transmission: The presence of porcine viruses that might infect humans cannot be definitely excluded. (5.4)
- Hypersensitivity Reactions: Monitor patients with known reactions to proteins of porcine origin. If symptoms occur, initiate appropriate medical management; consider the risks and benefits of continued treatment. (5.5)

6 ADVERSE REACTIONS

Most common adverse reactions (≥6%) are: headache, contusion, cough, and early satiety. (6.1)

To report SUSPECTED ADVERSE REACTIONS, contact Aimmune Therapeutics, Inc at 1-833-AIM2KNO (1-833-246-2566) or FDA at 1-800-FDA-1088 or www.fda.gov/medwatch.

FULL PRESCRIBING INFORMATION

1 INDICATIONS AND USAGE

ZENPEP® is indicated for the treatment of exocrine pancreatic insufficiency in adult and pediatric patients.

2 DOSAGE AND ADMINISTRATION

2.1 Important Dosing Information

ZENPEP is a mixture of enzymes including lipases, proteases, and amylases. ZENPEP dosing is based on lipase units.

- Use either an actual body weight or fat ingestion-based dosing scheme.
- Start at the lowest recommended dosage and individualize the dosage based on clinical symptoms, the degree of steatorrhea present, and the fat content of the diet. Changes in dosage may require an adjustment period of several days.
- Do not exceed 2,500 lipase units/kg/meal, 10,000 lipase units/kg/day, or 4,000 lipase units/g fat ingested/day in adult and pediatric patients greater than 12 months of age without further investigation [see Warnings and Precautions (5.1)].
- The total daily dosage in adult and pediatric patients greater than 12 months of age should reflect approximately three meals plus two or three snacks per day. With each snack, administer approximately half the prescribed ZENPEP dose for a meal.
- Do not substitute other pancreatic enzyme products for ZENPEP. When switching from another pancreatic enzyme product to ZENPEP, monitor patients for clinical symptoms of exocrine pancreatic insufficiency and titrate the dosage as needed.

2.2 Recommended Dosage

Adult and Pediatric Patients Greater than 12 Months of Age

The recommended oral initial starting dosage is:

- 500 lipase units/kg/meal for adult and pediatric patients 4 years of age and older.
- 1,000 lipase units/kg/meal for pediatric patients greater than 12 months of age to less than 4 years of age.

If signs and symptoms of malabsorption persist, increase the dosage. Titrate to either 2,500 lipase units/kg/meal, 10,000 lipase units/kg/day, or less than 4,000 lipase units/grams of fat ingested/day. Higher dosages may be administered if they are documented to be effective by fecal fat measures or an improvement in signs or symptoms of malabsorption including measures of nutritional status.

Pediatric Patients Birth to 12 Months of Age

The recommended oral dosage is 3,000 lipase units per 120 mL of formula or per breast-feeding.

2.3 Preparation and Administration Instructions

Instruct adult and pediatric patients greater than 12 months of age, or their caregivers, of the following:

- Take ZENPEP during meals or snacks. If a dose is missed, take the next dose with the next meal or snack.
- Swallow capsules whole.
- For patients who are unable to swallow intact capsules, carefully open the capsules and sprinkle the entire contents on a small amount of acidic soft food with a pH of 4.5 or less (e.g., commercially available preparations of applesauce, bananas, or pears). Consume the entire mixture immediately.
- Do not crush or chew ZENPEP capsules or capsule contents.
- Consume sufficient liquids (water or juice) to ensure complete swallowing of ZENPEP [see Warnings and Precautions (5.2)].

Instruct caregivers of pediatric patients birth to 12 months of age of the following:

- Immediately prior to each breast-feeding session or each administration of 120 mL of formula, carefully open one ZENPEP capsule (containing 3,000 USP units of lipase) and administer the entire contents using one of the following two methods:
  - Sprinkle on a small amount of acidic soft food with a pH of 4.5 or less (e.g., commercially available preparations of applesauce, bananas or pears) being careful not to crush the capsule contents. The entire mixture should be given to the infant immediately.
  - Sprinkle the capsule contents directly into the infant's mouth.
- Immediately administer additional breast milk or formula after ZENPEP to ensure complete swallowing of the capsule contents.
- Do not mix the ZENPEP capsule contents directly into a bottle of breast milk or formula.
- Do not crush ZENPEP capsule contents, and visually inspect the infant's mouth to ensure that no drug is retained in the mouth [see Warnings and Precautions (5.2)].
- If a dose is missed, administer the next dose with the next feeding.

3 DOSAGE FORMS AND STRENGTHS

Delayed-release capsules are available in the following strengths:

- 3,000 USP units of lipase; 10,000 USP units of protease; and 14,000 USP units of amylase in a two‑piece hypromellose capsule with a white opaque cap and white opaque body, and red imprint with "APTALIS 3"
- 5,000 USP units of lipase; 17,000 USP units of protease; and 24,000 USP units of amylase in a two‑piece hypromellose capsule with a white opaque cap and white opaque body, and blue imprint with "APTALIS 5"
- 10,000 USP units of lipase; 32,000 USP units of protease; and 42,000 USP units of amylase in a two-piece hypromellose capsule with a yellow opaque cap and white opaque body, and blue imprint with "APTALIS 10"
- 15,000 USP units of lipase; 47,000 USP units of protease; and 63,000 USP units of amylase in a two-piece hypromellose capsule with a red opaque cap and white opaque body, and blue imprint with "APTALIS 15"
- 20,000 USP units of lipase; 63,000 USP units of protease; and 84,000 USP units of amylase in a two-piece hypromellose capsule with a green opaque cap and white opaque body, and blue imprint with "APTALIS 20"
- 25,000 USP units of lipase; 79,000 USP units of protease; and 105,000 USP units of amylase in a two-piece hypromellose capsule with a blue opaque cap and white opaque body, and blue imprint with "APTALIS 25"
- 40,000 USP units of lipase; 126,000 USP units of protease; and 168,000 USP units of amylase in a two-piece hypromellose capsule with an orange opaque cap and white opaque body, and blue imprint with "APTALIS 40"
- 60,000 USP units of lipase; 189,600 USP units of protease; 252,600 USP units of amylase. Capsules have a powder blue opaque cap with two black stripes and white opaque body, black imprint with "APTALIS 60"

4 CONTRAINDICATIONS

None.

5 WARNINGS AND PRECAUTIONS

5.1 Fibrosing Colonopathy

Fibrosing colonopathy has been reported following treatment with pancreatic enzyme products. Fibrosing colonopathy is a rare serious adverse reaction initially described in association with use of high-dose pancreatic enzyme products, usually with use over a prolonged period of time and most commonly reported in pediatric patients with cystic fibrosis. Pancreatic enzyme products exceeding 6,000 lipase units/kg/meal have been associated with colonic stricture, a complication of fibrosing colonopathy, in pediatric patients less than 12 years of age. The underlying mechanism of fibrosing colonopathy remains unknown.

If there is a history of fibrosing colonopathy, monitor patients during treatment with ZENPEP because some patients may be at risk of progressing to colonic stricture formation. It is uncertain whether regression of fibrosing colonopathy occurs. Do not exceed the recommended dosage of either 2,500 lipase units/kg/meal, 10,000 lipase units/kg/day, or 4,000 lipase units/g fat ingested/day in adult and pediatric patients greater than 12 months of age without further investigation. Higher dosages may be administered if they are documented to be effective by fecal fat measures or an improvement in signs or symptoms of malabsorption including measures of nutritional status. Patients receiving dosages higher than 6,000 lipase units/kg/meal should be frequently monitored for symptoms of fibrosing colonopathy and the dosage decreased or titrated downward to a lower range if clinically appropriate [see Dosage and Administration (2.1)].

5.2 Irritation of the Oral Mucosa

Crushing or chewing ZENPEP capsules or mixing the capsule contents in foods having a pH greater than 4.5 can disrupt the protective enteric coating on the capsule contents and result in early release of enzymes, irritation of the oral mucosa, and/or loss of enzyme activity.

Instruct the patient or caregiver of the following:

- Swallow capsules whole. For patients who cannot swallow the capsules whole, the capsules can be opened, and the contents sprinkled on a small amount of acidic soft food with a pH of 4.5 or less (e.g., commercially available preparations of applesauce, bananas or pears).
- Do not crush or chew ZENPEP capsules or capsule contents.
- Consume sufficient liquids (juice, water, breast milk, or formula) immediately following administration of ZENPEP to ensure complete swallowing.
- Visually inspect the mouth of pediatric patients less than 12 months of age and of patients who are unable to swallow intact capsules to ensure no drug is retained in the mouth and irritation of the oral mucosa has not occurred [see Dosage and Administration (2.3)].

5.3 Hyperuricemia

Pancreatic enzyme products contain purines that may increase blood uric acid levels. High dosages have been associated with hyperuricosuria and hyperuricemia [see Overdosage (10)]. Consider monitoring blood uric acid levels in patients with gout, renal impairment, or hyperuricemia during treatment with ZENPEP.

5.4 Risk of Viral Transmission

ZENPEP is sourced from pancreatic tissue from swine used for food consumption. Although the risk that ZENPEP will transmit an infectious agent to humans has been reduced by testing for certain viruses during manufacturing and by inactivating certain viruses during manufacturing, there is a theoretical risk for transmission of viral disease, including diseases caused by novel or unidentified viruses. Thus, the presence of porcine viruses that might infect humans cannot be definitely excluded. However, no cases of transmission of an infectious illness associated with the use of porcine pancreatic extracts have been reported.

5.5 Hypersensitivity Reactions

Severe hypersensitivity reactions including anaphylaxis, asthma, hives, and pruritus have been reported with pancreatic enzyme products [see Adverse Reactions (6.2)]. If symptoms occur, initiate appropriate medical management.

Monitor patients with a known hypersensitivity reaction to proteins of porcine origin for hypersensitivity reactions during treatment with ZENPEP. The risks and benefits of continued ZENPEP treatment in patients with severe hypersensitivity reactions should be taken into consideration with the overall clinical needs of the patient.

6 ADVERSE REACTIONS

The following serious or otherwise important adverse reactions are described elsewhere in the labeling:

- Fibrosing Colonopathy [see Warnings and Precautions (5.1)]
- Irritation of the Oral Mucosa [see Warnings and Precautions (5.2)]
- Hyperuricemia [see Warnings and Precautions (5.3)]
- Risk of Viral Transmission [see Warnings and Precautions (5.4)]
- Hypersensitivity Reactions [see Warnings and Precautions (5.5)]

6.1 Clinical Trials Experience

Because clinical trials are conducted under widely varying conditions, adverse reaction rates observed in the clinical trials of a drug cannot be directly compared to the rates in the clinical trials of another drug and may not reflect the rates observed in clinical practice.

The data described below reflect exposure to ZENPEP in 53 adult and pediatric patients with exocrine pancreatic insufficiency due to cystic fibrosis in two clinical trials conducted [see Clinical Studies (14)]. In both trials, ZENPEP was administered at dosages of approximately 5,000 lipase units/kg/day for 19 to 42 days.

Study 1 was a randomized, double-blind, placebo-controlled, crossover study of 34 adult and pediatric patients, aged 7 to 23 years. Adverse reactions that were reported in at least 2 ZENPEP-treated patients (greater than or equal to 6%) and at a higher rate than in placebo-treated patients in Study 1 are shown in Table 1.

Table 1: Adverse Reactions [Reported in at least 2 ZENPEP-treated patients (greater than or equal to 6%) and at a higher rate than placebo-treated patients.] in a Clinical Trial of Adult and Pediatric Patients 7 Years of Age and Older with Exocrine Pancreatic Insufficiency due to Cystic Fibrosis (Study 1)
Adverse Reaction | ZENPEP N=34 n (%) | Placebo N=32 n (%)
Headache | 5 (15%) | 0
Contusion | 2 (6%) | 0
Cough | 2 (6%) | 0
Early Satiety | 2 (6%) | 0

Study 2 was an open-label, uncontrolled study of ZENPEP in 19 pediatric patients aged 1 to 6 years. The most commonly reported adverse reactions were gastrointestinal, including abdominal pain and steatorrhea.

The type and incidence of adverse reactions in Studies 1 and 2 were similar between pediatric patients and adults.

6.2 Postmarketing Experience

The following adverse reactions have been identified during post-approval use of ZENPEP or other pancreatic enzyme products. Because these reactions are reported voluntarily from a population of uncertain size, it is not always possible to reliably estimate their frequency or establish a causal relationship to drug exposure.

Eye Disorders

- blurred vision

Gastrointestinal Disorders

- fibrosing colonopathy and distal intestinal obstruction syndrome
- abdominal distension, abdominal pain, diarrhea, flatulence, constipation, and nausea

Immune System Disorders

- anaphylaxis, asthma, hives and pruritis

Investigations

- asymptomatic elevations of liver enzymes

Musculoskeletal System

- myalgia, muscle spasm

Skin and Subcutaneous Tissue Disorders

- urticaria and rash

8 USE IN SPECIFIC POPULATIONS

8.1 Pregnancy

Risk Summary

Published data from case reports with pancrelipase use in pregnant women have not identified a drug-associated risk of major birth defects, miscarriage or other adverse maternal or fetal outcomes. Pancrelipase is minimally absorbed systematically; therefore, maternal use is not expected to result in fetal exposure to the drug. Animal reproduction studies have not been conducted with pancrelipase.

The background risk of major birth defects and miscarriage for the indicated population is unknown. All pregnancies have a background risk of birth defect, loss, or other adverse outcomes. In the U.S. general population, the estimated background risk of major birth defects and miscarriage in clinically recognized pregnancies is 2 to 4% and 15 to 20%, respectively.

8.2 Lactation

Risk Summary

There are no data on the presence of pancrelipase in either human or animal milk, the effects on the breastfed infant or the effects on milk production. Pancrelipase is minimally absorbed systemically following oral administration, therefore maternal use is not expected to result in clinically relevant exposure of breastfed infants to the drug. The developmental and health benefits of breastfeeding should be considered along with the mother's clinical need for ZENPEP and any potential adverse effects on the breastfed infant from ZENPEP or from the underlying maternal conditions.

8.4 Pediatric Use

The safety and effectiveness of ZENPEP for the treatment of exocrine pancreatic insufficiency have been established in pediatric patients.

Use of ZENPEP for this indication is supported by an adequate and well-controlled trial in adult and pediatric patients 7 to 17 years of age (Study 1) along with supportive data from an open-label, single arm study in 19 pediatric patients 1 to 6 years of age (Study 2). Both study populations consisted of patients with exocrine pancreatic insufficiency due to cystic fibrosis. The safety in pediatric patients in Studies 1 and 2 were similar to that observed in adult patients [see Adverse Reactions (6.1) and Clinical Studies (14)].

Dosages exceeding 6,000 lipase units/kg/meal have been reported postmarketing to be associated with fibrosing colonopathy and colonic strictures in pediatric patients less than 12 years of age. If there is a history of fibrosing colonopathy, monitor patients during treatment with ZENPEP because some patients may be at risk of progressing to stricture formation. Do not exceed the recommended dosage of either 2,500 lipase units/kg/meal, 10,000 lipase units/kg/day, or 4,000 lipase units/g fat ingested/day in pediatric patients greater than 12 months of age without further investigation. [see Dosage and Administration (2.2) and Warnings and Precautions (5.1)].

Crushing or chewing ZENPEP capsules or mixing the capsule contents in foods having a pH greater than 4.5 can disrupt the protective enteric coating on the capsule contents and result in early release of enzymes, irritation of the oral mucosa, and/or loss of enzyme activity. Instruct the patient or caregiver of the following: consume sufficient liquids (juice, water, breast milk, or formula) to ensure complete swallowing, and visually inspect the mouth of pediatric patients less than 12 months of age to ensure that no drug is retained in the mouth and irritation of the oral mucosa has not occurred [see Dosage and Administration (2.3) and Warnings and Precautions (5.2)].

8.5 Geriatric Use

Clinical studies of ZENPEP did not include sufficient numbers of patients aged 65 years and over to determine whether they respond differently from younger patients. Other reported clinical experience has not identified differences in responses between patients aged 65 years and over and younger adult patients.

10 OVERDOSAGE

Chronic high dosages of pancreatic enzyme products have been associated with fibrosing colonopathy and colonic strictures [see Warnings and Precautions (5.1)]. High dosages of pancreatic enzyme products have been associated with hyperuricosuria and hyperuricemia [see Warnings and Precautions (5.3)].

11 DESCRIPTION

Pancrelipase is a pancreatic enzyme product consisting of a mixture of enzymes including lipases, proteases, and amylases, and is an extract derived from porcine pancreatic glands. The enteric-coated pellets in ZENPEP are formulated to release pancreatic enzymes at an approximate pH of 5.5 or greater.

ZENPEP (pancrelipase) delayed-release capsule for oral administration, include a two-piece shell containing light brown-colored enteric-coated pellets (1.8 to 1.9mm for 3,000 and 5,000 USP units of lipase, 2.2 to 2.5 mm for 10,000, 15,000, 20,000, 25,000, 40,000 and 60,000 USP units of lipase) and are available as follows:

3,000 USP units of lipase; 10,000 USP units of protease; and 14,000 USP units of amylase; delayed-release capsules have a white opaque cap and a white opaque body with imprint "APTALIS 3". The shells contain carnauba wax or talc, carrageenan, hypromellose, potassium chloride, titanium oxide, and water. The colorant of the printed ink is red iron oxide.

5,000 USP units of lipase; 17,000 USP units of protease; and 24,000 USP units of amylase; delayed-release capsules have a white opaque cap and a white opaque body with imprint "APTALIS 5". The shells contain carnauba wax or talc, carrageenan, hypromellose, potassium chloride, titanium oxide, and water. The colorant of the printed ink is FD&C Blue 2.

10,000 USP units of lipase; 32,000 USP units of protease; and 42,000 USP units of amylase; delayed-release capsules have a yellow opaque cap and a white opaque body with imprint "APTALIS 10". The shells contain carnauba wax or talc, carrageenan, hypromellose, potassium chloride, titanium oxide, water and yellow ferric oxide. The colorant of the printed ink is FD&C Blue 2.

15,000 USP units of lipase; 47,000 USP units of protease; and 63,000 USP units of amylase; delayed-release capsules have a red opaque cap and a white opaque body with imprint "APTALIS 15". The shells contain carnauba wax or talc, carrageenan, hypromellose, potassium chloride, red ferric oxide, titanium oxide, and water. The colorant of the printed ink is FD&C Blue 2.

20,000 USP units of lipase; 63,000 USP units of protease; and 84,000 USP units of amylase; delayed-release capsules have a green opaque cap and a white opaque body with imprint "APTALIS 20". The shells contain carnauba wax or talc, carrageenan, FD&C Blue #2, hypromellose, potassium chloride, titanium oxide, water, and yellow ferric oxide. The colorant of the printed ink is FD&C Blue 2.

25,000 USP units of lipase; 79,000 USP units of protease; and 105,000 USP units of amylase; delayed-release capsules have a blue opaque cap and a white opaque body with imprint "APTALIS 25". The shells contain carnauba wax or talc, carrageenan, FD&C Blue #2, hypromellose, potassium chloride, titanium oxide, and water. The colorant of the printed ink is FD&C Blue 2.

40,000 USP units of lipase; 126,000 USP units of protease; and 168,000 USP units of amylase; delayed-release capsules have an orange opaque cap and white opaque body, printed with "APTALIS 40". The shells contain FD&C Yellow #6, hypromellose, and titanium oxide. The colorant of the printed ink is FD&C Blue 2.

60,000 USP units of lipase; 189,600 USP units of protease; 252,600 USP units of amylase. Capsules have a powder blue opaque cap with two black stripes and white opaque body, printed with "APTALIS 60" The shells contain FD&C Blue #1, hypromellose, and titanium oxide. The colorant of the printed ink is black iron oxide.

ZENPEP (pancrelipase) delayed-release capsules include the following inactive ingredients: colloidal silicon dioxide, croscarmellose sodium, hydrogenated castor oil, hypromellose phthalate, magnesium stearate, microcrystalline cellulose, talc, and triethyl citrate.

12 CLINICAL PHARMACOLOGY

12.1 Mechanism of Action

Pancreatic enzyme products contain a mixture of lipases, proteases, and amylases that catalyze the hydrolysis of fats to monoglycerides, glycerol, and free fatty acids, protein into peptides and amino acids, and starch into dextrins and short chain sugars such as maltose and maltriose in the duodenum and proximal small intestine, thereby acting like digestive enzymes physiologically secreted by the pancreas.

12.2 Pharmacodynamics

For patients consuming a high fat diet in the clinical trials, the coefficient of fat absorption (CFA) was higher in patients who received ZENPEP compared to the placebo treatment group, indicating improved fat absorption [see Clinical Studies (14)].

12.3 Pharmacokinetics

Following oral administration, the lipases, proteases, and amylases released from ZENPEP are not absorbed from the gastrointestinal tract in appreciable amounts.

Drug Interactions

The lipases, proteases, and amylases of ZENPEP are not substrates of CYP enzymes or transporters. CYP enzymes or transporters mediated drug interactions are not expected.

14 CLINICAL STUDIES

Adult and Pediatric Patients 7 Years of Age and Older

Study 1 was a randomized, double-blind, placebo-controlled, crossover study of 34 patients, aged 7 to 23 years, with exocrine pancreatic insufficiency due to cystic fibrosis. The final analysis population was limited to 32 patients, who completed both double-blind treatment periods, and were included in the efficacy analysis population. Patients were randomized to receive ZENPEP or matching placebo for 6 to 7 days of treatment, followed by crossover to the alternate treatment for an additional 6 to 7 days. The mean exposure to ZENPEP during this study, including titration period and open label transition, was 30 days. The mean dosage during the controlled treatment periods ranged from a mean dose of 3,900 lipase units/kg/day to 5,700 lipase units/kg/day. All patients consumed a high-fat diet (greater than or equal to 100 grams of fat per day) during the treatment period. The population was nearly evenly distributed in biological sex, and approximately 96% of patients were White.

Coefficient of Fat Absorption Endpoint and Results

The primary efficacy endpoint was the mean difference in the coefficient of fat absorption (CFA) between ZENPEP and placebo treatment. The CFA was determined by a 72-hour stool collection during both treatments, when both fat excretion and fat ingestion were measured. Each patient's CFA during placebo treatment was used as their no-treatment CFA value.

Mean CFA was 88% with ZENPEP treatment compared to 63% with placebo treatment. The mean difference in CFA was 26 percentage points in favor of ZENPEP treatment with 95% Confidence Interval of (19, 32) and p≤0.001.

Subgroup analyses of the CFA results showed that mean change in CFA was greater in patients with lower no-treatment (placebo) CFA values than in patients with higher no-treatment (placebo) CFA values. There were similar responses to ZENPEP by age and biological sex.

Pediatric Patients 1 to 6 Years of Age

Study 2 was an open-label, uncontrolled study of 19 pediatric patients, aged 1 to 6 years (mean age 4 years), with exocrine pancreatic insufficiency due to cystic fibrosis. Approximately half of the patients were aged 1 to 3 years. Study 2 compared a measurement of fat malabsorption, spot fecal fat testing, before (while receiving therapy with another pancreatic enzyme product) and after oral administration of ZENPEP capsules with each meal or snack.

After a 4 to 14 day screening period during which patients remained on their current pancreatic enzyme product, patients were switched to ZENPEP at individually titrated dosages ranging between 2,300 and 10,000 lipase units/kg/day (not to exceed 2,500 lipase units/kg/meal) for 14 days. The mean ZENPEP dosage was approximately 5,000 lipase unit/kg/day. There was no wash-out period. Overall, patients showed similar control of fat malabsorption by spot fecal fat testing when switched from their current pancreatic enzyme product to ZENPEP treatment at a similar dosage.

16 HOW SUPPLIED/STORAGE AND HANDLING

ZENPEP (pancrelipase) delayed-release capsules containing light, brown-colored delayed-release pancrelipase are supplied as follows:

Strength | Description | Supplied As | NDC Number
3,000 USP units of lipase; 10,000 USP units of protease; 14,000 units of amylase | two-piece hypromellose capsule with white opaque cap and white body with a red radial print and printed with "APTALIS 3" | Bottles of 100 | 73562-113-01
5,000 USP units of lipase; 17,000 USP units of protease; 24,000 units of amylase | two-piece hypromellose capsule with a white opaque cap and white body with a blue radial print and printed with "APTALIS 5" | Bottles of 100 | 73562-115-01
10,000 USP units of lipase; 32,000 units of protease; 42,000 units of amylase | two-piece hypromellose capsule with a yellow opaque cap and white body with a blue radial print and printed with "APTALIS 10" | Bottles of 100 | 73562-110-01
15,000 USP units of lipase; 47,000 units of protease; 63,000 units of amylase | two-piece hypromellose capsule with a red opaque cap and white body with a blue radial print and printed with "APTALIS 15" | Bottles of 100 | 73562-111-01
20,000 USP units of lipase; 63,000 units of protease; 84,000 units of amylase | two-piece hypromellose capsule with a green opaque cap and white body with a blue radial print and printed with "APTALIS 20" | Bottles of 100 | 73562-112-01
25,000 USP units of lipase; 79,000 units of protease; 105,000 units of amylase | two-piece hypromellose capsule with a blue opaque cap and white body with a blue radial print and printed with "APTALIS 25" | Bottles of 100 | 73562-116-01
40,000 USP units of lipase; 126,000 units of protease; 168,000 units of amylase | two-piece hypromellose capsule with an orange opaque cap and white body with a blue radial print and printed with "APTALIS 40" | Bottles of 100 | 73562-114-01
60,000 USP units of lipase; 189,600 units of protease; 252,600 units of amylase | two-piece hypromellose capsule with powder blue opaque cap with two black stripes and white body with a black radial print and printed with "APTALIS 60" | Bottles of 100 | 73562-117-01

Storage and Handling

Original container:

Store at room temperature, 20°C to 25°C (68°F to 77°F) and protect from moisture. Brief excursions permitted to 15°C to 40°C (59°F to104°F) for 24 hours. After opening, keep bottle tightly closed between uses to protect from moisture.

Zenpep is supplied in bottles containing a desiccant.

Repackaged HDPE container:

Dispense in tight container (USP). Store at up to 30°C (86°F) for up to 6 months and protect from moisture. Brief excursions permitted to 15°C to 40°C (59°F to 104°F) for up to 30 days. Protect from moisture. After opening, keep bottle tightly closed between uses to protect from moisture.

17 PATIENT COUNSELING INFORMATION

Advise the patient or caregiver to read the FDA-approved patient labeling (Medication Guide).

Fibrosing Colonopathy

Advise the patient or caregiver that fibrosing colonopathy has been reported with high dosages of pancreatic enzyme products, usually with use over a prolonged period of time and in pediatric patients with cystic fibrosis. Colonic stricture has been reported in pediatric patients less than 12 years of age. Advise patients and caregivers that if signs and symptoms of colon stricture formation occur (e.g., stomach area (abdominal) pain, bloating, trouble passing stool (constipation), nausea, vomiting, diarrhea) to immediately contact their healthcare provider [see Warnings and Precautions (5.1)].

Hyperuricemia

Advise the patient or caregiver that hyperuricemia may occur in patients with gout or renal impairment and to contact the healthcare provider if they experience pain, stiffness, redness or swelling of their joints [see Warnings and Precautions (5.3)].

Hypersensitivity Reactions

Inform the patient or caregiver that severe hypersensitivity reactions, including anaphylaxis asthma, hives, and pruritus, have been reported with use of pancreatic enzyme products. Seek medical attention if signs or symptoms of a hypersensitivity reaction develop [see Warnings and Precautions (5.5)].

Dosage

Advise the patient or caregiver to take ZENPEP as prescribed, and to contact the healthcare provider if signs and symptoms of malabsorption persist [see Dosage and Administration (2.2)].

Administration

Instruct the patient or caregiver as follows:

- Take ZENPEP with meals or snacks.
- Swallow capsules whole.
- For adult and pediatric patients who are unable to swallow intact capsules, the capsule contents may be sprinkled on a small amount of acidic soft food with a pH of 4.5 or less (e.g., commercially available preparations of applesauce, bananas, or pears). For pediatric patients birth to 12 months of age, ZENPEP capsules can also be opened, and the capsule contents sprinkled directly into the infant's mouth.
- Consume sufficient liquids (juice, water, breast milk, or formula) and visually inspect an infant's mouth to ensure complete swallowing of ZENPEP capsules or capsule contents [see Warnings and Precautions (5.2)].
- Do not crush or chew ZENPEP capsules or capsule contents.
- Do not mix the ZENPEP capsule contents directly into a bottle of breast milk or formula.

Storage

Instruct the patient or caregiver as follows:

- Keep ZENPEP in a dry place and protect from moisture and heat.
- After opening, keep bottle tightly closed between uses to protect from moisture.
- Keep the desiccant in the bottle, if present. The desiccant packet should not be eaten or thrown away.

Manufactured by:
Aimmune Therapeutics, Inc.
1007 US Highway 202/206,
Bridgewater, NJ 08807, USA

US License No. 2109

For further information, please call Aimmune Therapeutics at 1-833-AIM2KNO (1-833-246-2566)

©2025 Nestlé

All trademarks are owned by Société des Produits Nestlé S.A., Vevey, Switzerland or used with permission.

Patented. See www.nestlehealthscience.us/patents.

MEDICATION GUIDE
ZENPEP® (ZEN-pep)
(pancrelipase)
delayed-release capsules, for oral use

What is the most important information I should know about ZENPEP?

ZENPEP may increase your chance of having a rare bowel disorder called fibrosing colonopathy especially if taken at a high dose for a long time in children with cystic fibrosis. This condition is serious and may require surgery. The risk of having this condition may be reduced by following the dosing instructions that your doctor gave you. Call your doctor right away if you have any unusual or severe:

- Stomach area (abdominal) pain
- Bloating
- Trouble passing stool (having bowel movements)
- Nausea, vomiting, or diarrhea

Take ZENPEP exactly as prescribed by your doctor. Do not take more ZENPEP than directed by your doctor.

What is ZENPEP?

- ZENPEP is a prescription medicine used to treat people who cannot digest food normally because their pancreas does not make enough enzymes.
- ZENPEP contains a mixture of digestive enzymes including lipases, proteases, and amylases from pig pancreas.
- ZENPEP is safe and effective in adults and children.

Before taking ZENPEP, tell your doctor about all your medical conditions, including if you:

- are allergic to pork (pig) products.
- have a history of blockage of your intestines, or scarring or thickening of your bowel wall (fibrosing colonopathy).
- have gout, kidney disease, or high blood uric acid (hyperuricemia).
- have trouble swallowing capsules.
- have any other medical condition.
- are pregnant or plan to become pregnant.
- are breastfeeding or plan to breastfeed. It is not known if ZENPEP passes into your breast milk. Talk to your doctor about the best way to feed your baby if you take ZENPEP.

Tell your doctor about all the medicines you take, including prescription and over-the-counter medicines, vitamins, and herbal supplements.
Know the medicines you take. Keep a list of them and show it to your doctor and pharmacist when you get a new medicine.

How should I take ZENPEP?

- Take ZENPEP exactly as your doctor tells you. Contact your doctor if you continue to have signs and symptoms of malabsorption (not absorbing nutrients from food) such as abdominal pain, abdominal distention, bloating, fatty stools, or weight loss. Your dose may need to be changed.
- You should not switch ZENPEP with any other pancreatic enzyme product without first talking to your doctor.
- Do not take more capsules in a day than the number your doctor tells you (total daily dose).
- Always take ZENPEP with a meal or snack. If you eat a lot of meals or snacks in a day, be careful not to go over your total daily dose.
- ZENPEP capsules should be swallowed whole. Do not crush or chew the ZENPEP capsules or its contents and do not hold the capsule contents in your mouth. Crushing or chewing the ZENPEP capsules may cause irritation in your mouth or change the way ZENPEP works in your body.

Giving ZENPEP to Adults and Children 12 Months of Age and Older:

- Swallow ZENPEP capsules whole and take them with enough liquid (water or juice) to swallow them right away.
- If you have trouble swallowing capsules, open the capsules and sprinkle the entire contents on a small amount of acidic soft food such as applesauce, bananas or pears. Ask your doctor about other foods you can mix with ZENPEP.
- If you sprinkle ZENPEP on food, swallow it right after you mix it. Do not store ZENPEP that is mixed with food.
- Swallow the ZENPEP and food mixture right away followed with water or juice. Make sure the medicine is swallowed completely.
- If you forget to take ZENPEP, call your doctor or wait until your next meal and take your usual number of capsules. Do not make up for missed doses. Take your next dose at the usual time.

Giving ZENPEP to Infants (Children from Birth to 12 Months of Age):
The 2 ways to give ZENPEP to infants (children from birth to 12 months of age), which are described below:
a) Giving with an Acidic Soft Food

1. Before each breastfeeding session or each time you give 120 mL of formula, carefully open the capsule and sprinkle the entire contents of the capsule in a small amount of acidic soft food (such as, store bought preparations of applesauce, bananas or pears)
2. Mix the capsule contents evenly through the food. Be careful not to crush the ZENPEP capsule contents while mixing.
3. Give the entire mixture to the infant right away. Do not store the ZENPEP mixture or save for later use.
4. Do not mix the ZENPEP capsule contents directly into a bottle of breast milk or formula.
5. Give your infant enough formula or breastfeed your infant right away to completely swallow the ZENPEP food mixture.
6. Look into your infant's mouth to make sure that all of the medicine has been swallowed.
7. Throw away the empty ZENPEP capsule.

b) Giving Directly Into the Infant's Mouth Before Breastfeeding or Formula Feeding

1. Before each breastfeeding session or each time you give 120 mL of formula, carefully open the ZENPEP capsule and sprinkle the capsule contents directly into the infant's mouth.
2. Do not mix the ZENPEP capsule contents directly into a bottle of breast milk or formula.
3. Give your infant additional breast milk or formula right after ZENPEP to completely swallow the ZENPEP capsule contents.
4. Look in your infant's mouth to make sure that all the medicine has been swallowed.
5. Throw away the empty ZENPEP capsule.

- If a dose is missed, give the next dose with the next feeding.

What are possible side effects of ZENPEP?
ZENPEP may cause serious side effects, including:

- See "What is the most important information I should know about ZENPEP?"
- Irritation of the inside of your mouth. This can happen if ZENPEP is not swallowed completely.
- Increase in blood uric acid levels (hyperuricemia). This may happen in people with gout, kidney problems, or those who take high doses of pancrelipase, the active ingredient in ZENPEP. Call your doctor if you have pain, stiffness, redness or swelling of your joints.
- Severe allergic reactions. Severe allergic reactions have happened in people taking pancreatic enzyme products like ZENPEP. Stop taking ZENPEP and get emergency treatment right away if you have any of these symptoms:
  trouble with breathing, skin rashes, swollen lips, or itching.

The most common side effects of ZENPEP include:

- Headache
- Bruising
- Cough
- Feeling full after eating a small amount of food

Other Possible Side Effects:
ZENPEP and other pancreatic enzyme products are made from the pancreas of pigs, the same pigs people eat as pork. These pigs may carry viruses. Although it has never been reported, it may be possible for a person to get a viral infection from taking pancreatic enzyme products that come from pigs.
Tell your doctor if you have any side effect that bothers you or does not go away.
These are not all the possible side effects of ZENPEP.
Call your doctor for medical advice about side effects. You may report side effects to FDA at 1-800-FDA-1088.
You may also report side effects to Aimmune Therapeutics, Inc at 1-833-AIM2KNO (1-833-246-2566).

How do I store ZENPEP?

- Store ZENPEP at room temperature between 68ºF to 77ºF (20°C to 25°C). Avoid heat.
- After opening the bottle, keep it closed tightly between uses to protect from moisture.
- Do not eat or throw away the packet (desiccant) in your medicine bottle, if present. Keep it in the bottle. This packet will protect your medicine from moisture.
- Store ZENPEP in a dry place.

Keep ZENPEP and all medicines out of the reach of children.

General information about the safe and effective use of ZENPEP.
Medicines are sometimes prescribed for purposes other than those listed in a Medication Guide. Do not use ZENPEP for a condition for which it was not prescribed. Do not give ZENPEP to other people, even if they have the same symptoms you have. It may harm them.
You can ask your pharmacist or doctor for information about ZENPEP that is written for health professionals.

What are the ingredients in ZENPEP?
Active ingredients: lipase, protease, amylase
Inactive ingredients: colloidal silicon dioxide, croscarmellose sodium, hydrogenated castor oil, hypromellose phthalate, magnesium stearate, microcrystalline cellulose, talc, and triethyl citrate in hypromellose capsules.
The red radial imprinting on the 3,000 capsule strength contains red iron oxide as colorant.
The blue radial imprinting on the 5,000, 10,000, 15,000, 20,000, 25,000, and 40,000 capsule strengths contains FD&C Blue #2 as colorant.
The black radial imprinting on the 60,000 capsule strength contains black iron oxide as colorant.
Capsule shell ingredients:

- 3,000 USP units and 5,000 USP units of lipase contain carnauba wax or talc, carrageenan, hypromellose, potassium chloride, titanium oxide, and water.
- 10,000 USP units of lipase contain carnauba wax or talc, carrageenan, hypromellose, potassium chloride, titanium oxide, water and yellow ferric oxide.
- 15,000 USP units of lipase contain carnauba wax or talc, carrageenan, hypromellose potassium chloride, red ferric oxide, titanium oxide, and water.
- 20,000 USP units of lipase contain carnauba wax or talc, carrageenan, FD&C Blue #2, hypromellose, potassium chloride, titanium oxide, water, and yellow ferric oxide.
- 25,000 USP units of lipase contain carnauba wax or talc, carrageenan, FD&C Blue #2 hypromellose, potassium chloride, titanium oxide, and water.
- 40,000 USP units of lipase contain FD&C Yellow #6, hypromellose, and titanium oxide.
- 60,000 USP units of lipase contain FD&C Blue #1, hypromellose and titanium oxide.

Manufactured by:
Aimmune Therapeutics, Inc.
1007 US Highway 202/206,
Bridgewater, NJ 08807, USA
Product of Germany
US License No. 2109
For further information, please go to www.ZENPEP.com or call Aimmune Therapeutics, Inc at 1-833-AIM2KNO (1-833-246-2566)
©2025 Nestlé
All trademarks are owned by Société des Produits Nestlé S.A., Vevey, Switzerland or used with permission.

This Medication Guide has been approved by the U.S. Food and Drug Administration.

Revised 07/2025

PRINCIPAL DISPLAY PANEL - 100 Capsule Bottle Label - NDC 73562-113-01

NDC 73562-113-01

pancrelipase

Zenpep®
DELAYED-RELEASE CAPSULES

Rx only

DOSE BY
LIPASE
UNITS:
Lipase 3,000 USP units
Protease 10,000 USP units
Amylase 14,000 USP units

Dispense enclosed Medication Guide to each patient

100 Delayed-Release Capsules

PRINCIPAL DISPLAY PANEL - 100 Capsule Bottle Label - NDC 73562-115-01

NDC 73562-115-01

pancrelipase

Zenpep®
DELAYED-RELEASE CAPSULES

Rx only

DOSE BY
LIPASE
UNITS:
Lipase 5,000 USP units
Protease 17,000 USP units
Amylase 24,000 USP units

Dispense enclosed Medication Guide to each patient

100 Delayed-Release Capsules

PRINCIPAL DISPLAY PANEL - 100 Capsule Bottle Label - NDC 73562-110-01

NDC 73562-110-01

pancrelipase

Zenpep®
DELAYED-RELEASE CAPSULES

Rx only

DOSE BY
LIPASE
UNITS:
Lipase 10,000 USP units
Protease 32,000 USP units
Amylase 42,000 USP units

Dispense enclosed Medication Guide to each patient

100 Delayed-Release Capsules

PRINCIPAL DISPLAY PANEL - 100 Capsule Bottle Label - NDC 73562-111-01

NDC 73562-111-01

pancrelipase

Zenpep®
DELAYED-RELEASE CAPSULES

Rx only

DOSE BY
LIPASE
UNITS:
Lipase 15,000 USP units
Protease 47,000 USP units
Amylase 63,000 USP units

Dispense enclosed Medication Guide to each patient

100 Delayed-Release Capsules

PRINCIPAL DISPLAY PANEL - 100 Capsule Bottle Label - NDC 73562-112-01

NDC 73562-112-01

pancrelipase

Zenpep®
DELAYED-RELEASE CAPSULES

Rx only

DOSE BY
LIPASE
UNITS:
Lipase 20,000 USP units
Protease 63,000 USP units
Amylase 84,000 USP units

Dispense enclosed Medication Guide to each patient

100 Delayed-Release Capsules

PRINCIPAL DISPLAY PANEL - 100 Capsule Bottle Label - NDC 73562-116-01

NDC 73562-116-01

pancrelipase

Zenpep®
DELAYED-RELEASE CAPSULES

Rx only

DOSE BY
LIPASE
UNITS:
Lipase 25,000 USP units
Protease 79,000 USP units
Amylase 105,000 USP units

Dispense enclosed Medication Guide to each patient

100 Delayed-Release Capsules

PRINCIPAL DISPLAY PANEL - 100 Capsule Bottle Label - NDC 73562-114-01

NDC 73562-114-01

pancrelipase

Zenpep®
DELAYED-RELEASE CAPSULES

Rx only

DOSE BY
LIPASE
UNITS:
Lipase 40,000 USP units
Protease 126,000 USP units
Amylase 168,000 USP units

Dispense enclosed Medication Guide to each patient

100 Delayed-Release Capsules

PRINCIPAL DISPLAY PANEL - 100 Capsule Bottle Label - NDC 73562-117-01

NDC 73562-117-01

pancrelipase

Zenpep®
DELAYED-RELEASE CAPSULES

Rx only

DOSE BY
LIPASE
UNITS:
Lipase 60,000 USP units
Protease 189,600 USP units
Amylase 252,600 USP units

Dispense enclosed Medication Guide to each patient

100 Delayed-Release Capsules